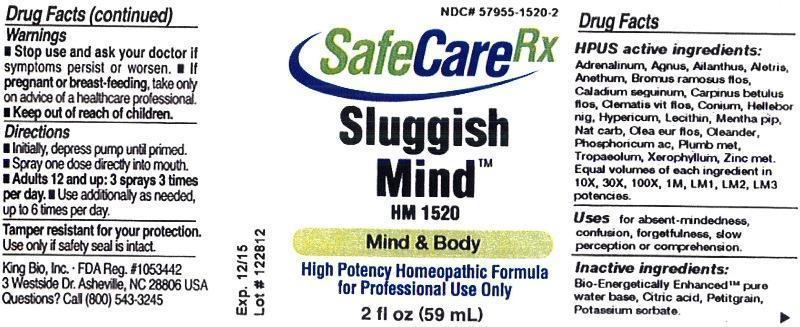 DRUG LABEL: Sluggish Mind
NDC: 57955-1520 | Form: LIQUID
Manufacturer: King Bio Inc.
Category: homeopathic | Type: HUMAN PRESCRIPTION DRUG LABEL
Date: 20130226

ACTIVE INGREDIENTS: EPINEPHRINE 10 [hp_X]/59 mL; CHASTE TREE 10 [hp_X]/59 mL; AILANTHUS ALTISSIMA FLOWERING TWIG 10 [hp_X]/59 mL; ALETRIS FARINOSA ROOT 10 [hp_X]/59 mL; DILL 10 [hp_X]/59 mL; BROMUS RAMOSUS FLOWER 10 [hp_X]/59 mL; DIEFFENBACHIA SEGUINE 10 [hp_X]/59 mL; CARPINUS BETULUS FLOWERING TOP 10 [hp_X]/59 mL; CLEMATIS VITALBA FLOWER 10 [hp_X]/59 mL; CONIUM MACULATUM FLOWERING TOP 10 [hp_X]/59 mL; HELLEBORUS NIGER ROOT 10 [hp_X]/59 mL; HYPERICUM PERFORATUM 10 [hp_X]/59 mL; EGG PHOSPHOLIPIDS 10 [hp_X]/59 mL; MENTHA PIPERITA 10 [hp_X]/59 mL; SODIUM CARBONATE 10 [hp_X]/59 mL; OLEA EUROPAEA FLOWER 10 [hp_X]/59 mL; NERIUM OLEANDER LEAF 10 [hp_X]/59 mL; PHOSPHORIC ACID 10 [hp_X]/59 mL; LEAD 10 [hp_X]/59 mL; TROPAEOLUM MAJUS 10 [hp_X]/59 mL; XEROPHYLLUM ASPHODELOIDES 10 [hp_X]/59 mL; ZINC 10 [hp_X]/59 mL
INACTIVE INGREDIENTS: WATER; CITRIC ACID MONOHYDRATE; CITRUS AURANTIUM LEAFY TWIG OIL; POTASSIUM SORBATE

Sluggish Mind

Active Ingredients

HPUS active ingredients:

Adrenalinum, Agnus Castus, Ailanthus glandulosus, Aletris farinosa, Anethum graveolens, Bromus ramosus, flos, Caladium seguinum, Carpinus betulus, flos, Clematis vitalba, flos, Clematis vitalba, flos, Conium maculatum, Helleborus niger, Conium maculatum, Helleborus niger, Hypericum perforatum, Lecithin, Mentha piperita, Natrum carbonicum, Olea europaea, flos, Oleander, Phosphoricum acidum, Plumbum metallicum, Tropaeolum majus, Xerophyllum asphodeloides, Zincum metallicum.

Equal volumes of each ingredient in 10X, 30X, 100X, 1M, LM1, LM2, LM3 potencies.

Inactive Ingredients

Bio-Energetically Enhanced ™ pure water base, Citric acid, Petitgrain, Potassium sorbate.

Purpose

Uses for:

- absent-mindedness
- confusion
- forgetfulness
- slow perception or comprehension

Warnings

- Stop use and ask your doctor if symptoms persist or worsen.
- If pregnant or breast-feeding, take only on advice of a healthcare professional.
- Keep out of reach of children.

Tamper resistant for your protection. Use only if safety seal is intact

Keep out of reach of children.

Dosage and Administration

Directions

- Initially, depress pump until primed.
- Spray one dose directly into mouth.
- Adults 12 and up: 3 sprays 3 times per day.
- Use additionally as needed, up to 6 times per day.

Indications and Usage

Uses for absent-mindedness, confusion, forgetfulness, slow perception or comprehension.